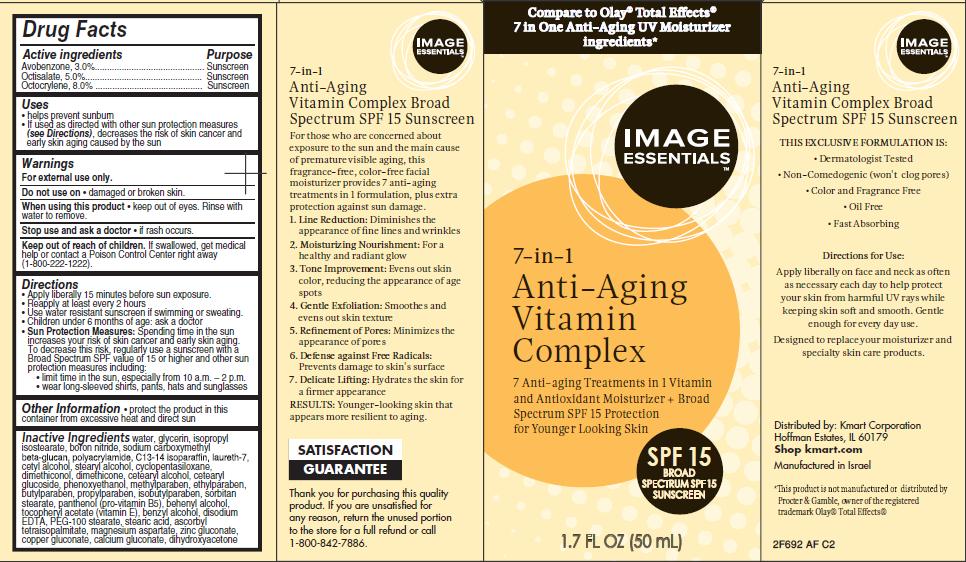 DRUG LABEL: Anti-Aging Vitamin Complex 7-in-1 Broad Spectrum SPF15 Sunscreen
NDC: 49738-694 | Form: LOTION
Manufacturer: Kmart Corporation
Category: otc | Type: HUMAN OTC DRUG LABEL
Date: 20130910

ACTIVE INGREDIENTS: AVOBENZONE 3 g/100 mL; OCTISALATE 5 g/100 mL; OCTOCRYLENE 8 g/100 mL
INACTIVE INGREDIENTS: WATER; GLYCERIN; ISOPROPYL ISOSTEARATE; BORON NITRIDE; POLYACRYLAMIDE (10000 MW); C13-14 ISOPARAFFIN; LAURETH-7; CETYL ALCOHOL; STEARYL ALCOHOL; CYCLOMETHICONE 5; DIMETHICONOL (100000 CST); DIMETHICONE; CETOSTEARYL ALCOHOL; CETEARYL GLUCOSIDE; PHENOXYETHANOL; METHYLPARABEN; ETHYLPARABEN; BUTYLPARABEN; PROPYLPARABEN; ISOBUTYLPARABEN; SORBITAN MONOSTEARATE; PANTHENOL; DOCOSANOL; .ALPHA.-TOCOPHEROL ACETATE; BENZYL ALCOHOL; TROLAMINE; EDETATE DISODIUM; PEG-100 STEARATE; STEARIC ACID; ASCORBYL TETRAISOPALMITATE; MAGNESIUM ASPARTATE; ZINC GLUCONATE; COPPER GLUCONATE; CALCIUM GLUCONATE; DIHYDROXYACETONE

Image Essentials® Anti-Aging Vitamin Complex Broad Spectrum SPF15 Sunscreen

Active ingredient

Avobenzone 3.0%

Octisalate 5.0%

Octocrylene 8.0%

Purpose

Sunscreen

Uses

- helps prevent sunburn
- If used as directed with other sun protection measures (see Directions), decreases the risk of skin cancer and early skin aging caused by the sun

Warnings

For external use only.

Do not use on

- damaged or broken skin.

When using this product

- keep out of eyes. Rinse with water to remove.

Stop use and ask a doctor

- if rash occurs.

Keep Out of Reach of Children.

If swallowed, get medical help or contact a Poison Control Center right away (1-800-222-1222).

Directions

- Apply liberally 15 minutes before sun exposure.
- Reapply at least every 2 hours
- Use a water resistant sunscreen if swimming or sweating
- Children under 6 months of age: ask a doctor
- Sun Protection Measures: Spending time in the sun increases your risk of skin cancer and early skin aging. To decrease this risk, regularly use a sunscreen with a Broad Spectrum SPF value of 15 or higher and other sun protection measures including:
  - limit time in the sun, especially from 10 a.m. - 2 p.m.
  - wear long-sleeved shirts, pants, hats and sunglasses

Other Information

- protect the product in this container from excessive heat and direct sun

Inactive Ingredients

water, glycerin, isopropyl isostearate, boron nitride, sodium carboxymethyl beta-glucan, polyacrylamide, C13-14 isoparaffin, laureth-7, cetyl alcohol, stearyl alcohol, cyclopentasiloxane, dimethiconol, dimethicone, cetearyl alcohol, cetearyl glucoside, phenoxyethanol, methylparaben, ethylparaben, butylparaben, propylparaben, isobutylparaben, sorbitan stearate, panthenol (vitamin B5), behenyl alcohol, tocopheryl acetate (vitamin E), benzyl alcohol, , disodium EDTA, PEG-100 stearate, stearic acid, ascorbyl tetraisopalmitate, magnesium aspartate, zinc gluconate, copper gluconate, calcium gluconate, dihydroxyacetone

Package/Label Principal Display Panel

Image Essentials® 7-in-1 Anti -Aging Vitamin Complex

7 Anti-aging Treatments in 1 Vitamin and Antioxidant Moisturizer + Broad Spectrum SPF 15 Protection for Younger Looking Skin

Compare to Olay® Total Effects®
7 in One Anti-Aging UV Moisturizer
ingredients*

SPF 15 Broad Spectrum Sunscreen

1.7 FL OZ (50 mL)

*This product is not manufactured or distributed by Procter & Gamble, owner of the registered trademark Olay® Total Effects.

Distributed by:
Kmart Corporation
Hoffman Estates, IL 60179
Shop kmart.com
Manufactured in Israel

2F692 AF C2

Carton Label